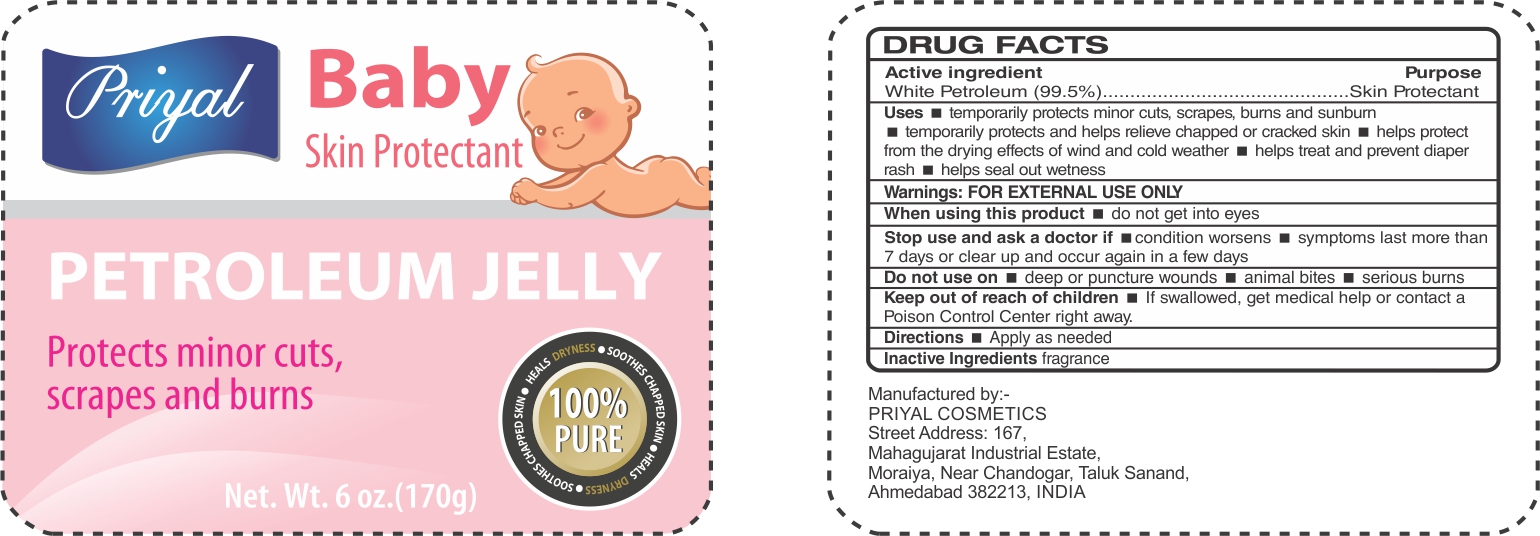 DRUG LABEL: Priyal Aloe Baby
NDC: 72822-006 | Form: OINTMENT
Manufacturer: Priyal Cosmetics
Category: otc | Type: HUMAN OTC DRUG LABEL
Date: 20200219

ACTIVE INGREDIENTS: PETROLATUM 99.5 g/100 g
INACTIVE INGREDIENTS: WATER

baby JELLY

Active Ingredient

White Petrolatum USP 99.5%

Purpose

Skin Protectant

USES

Temporarily protects minor cuts, scrapes, burns and sunburn

Temporarily protects and helps relieve chapped or cracked skin

helps protect from the drying effects of wind and cold weather

helps treat and prevent diaper rash

helps seal out wetness

Warnings

FOR EXTERNAL USE ONLY

When using this product

do not get into eyes

Stop use and ask a doctor if

- condition worsens
- symptoms last more than 7 days or clear up and occur again in few days

Do not use on

- deep or puncture wounds
- animal bites
- serious burns

Keep out of reach of children

- If swallowed, get medical help or contact a Poison Control center right away

Directions

Apply as needed

Inactive ingredient

fragrance